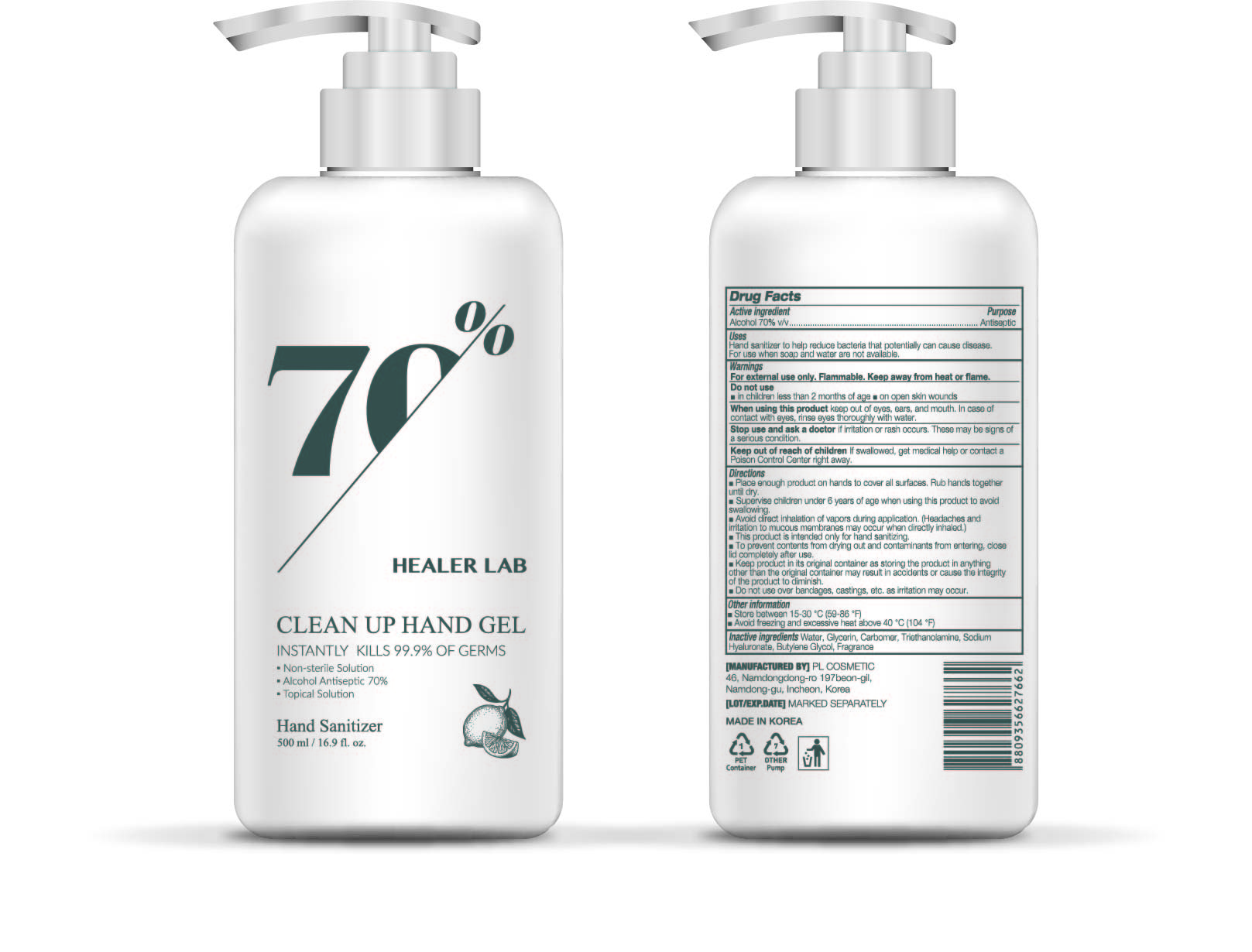 DRUG LABEL: HEALER LAB CLEAN UP HAND Gel
NDC: 74339-0500 | Form: GEL
Manufacturer: PL COSMETIC
Category: otc | Type: HUMAN OTC DRUG LABEL
Date: 20200401

ACTIVE INGREDIENTS: ALCOHOL 350 mL/500 mL
INACTIVE INGREDIENTS: GLYCERIN; CARBOMER HOMOPOLYMER, UNSPECIFIED TYPE; WATER; BUTYLENE GLYCOL; HYALURONATE SODIUM; TROLAMINE

[HEALER LAB CLEAN UP HAND Gel ] 500 ml : 74339-0500